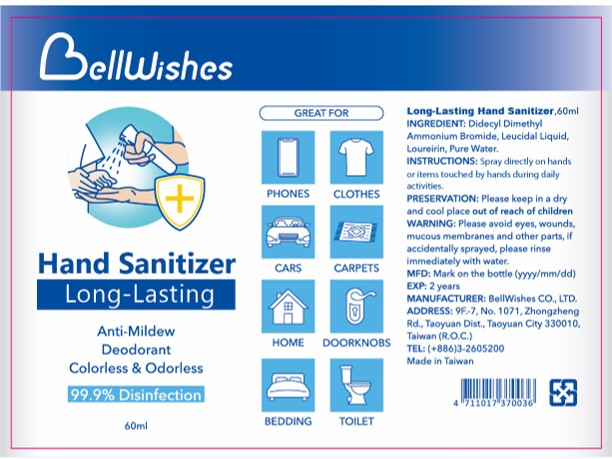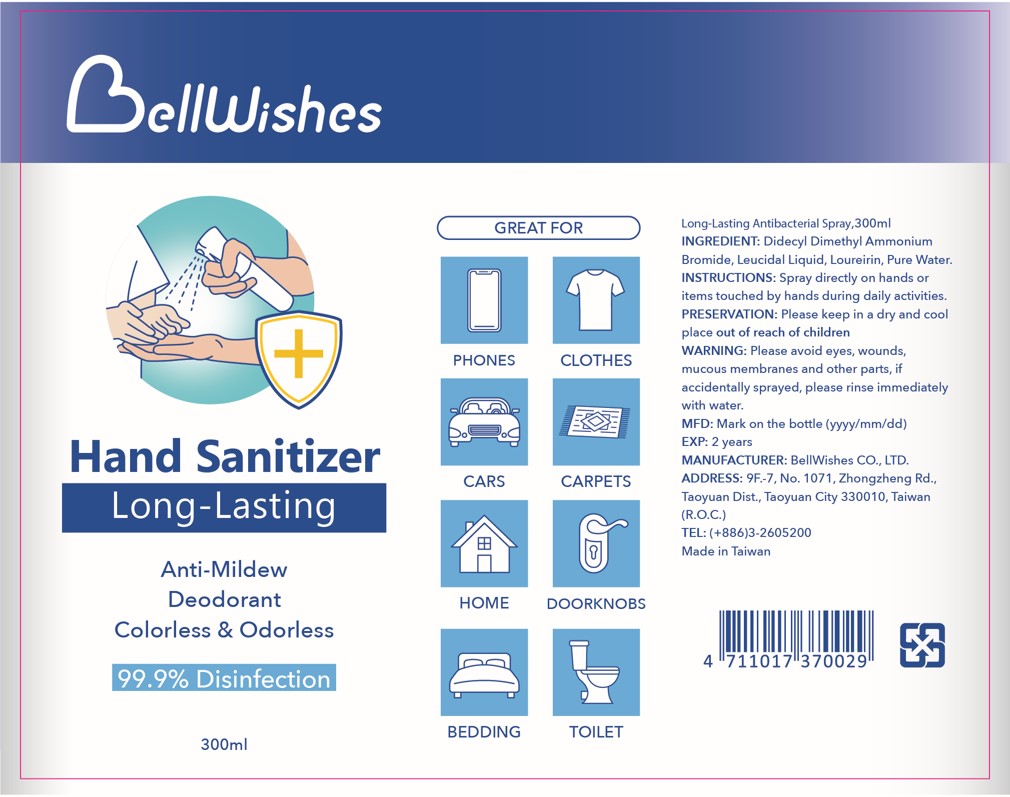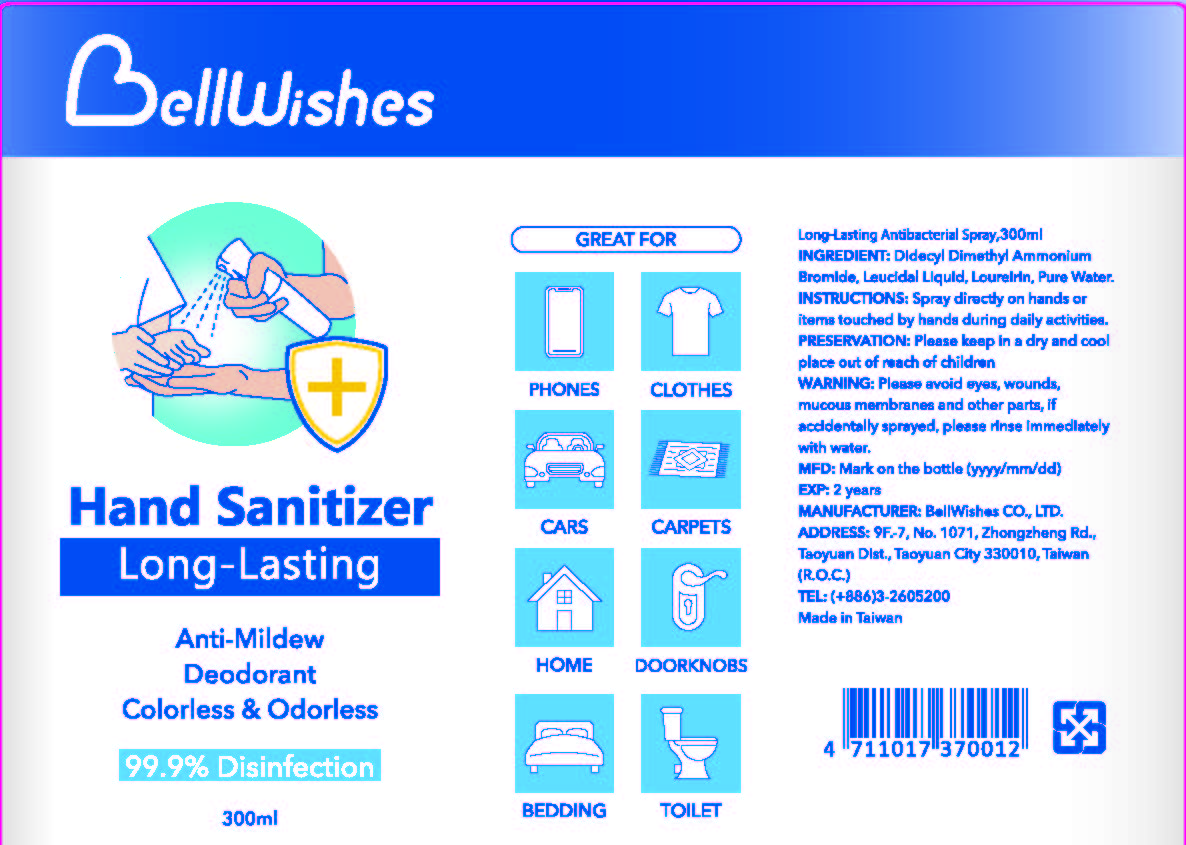 DRUG LABEL: Hand Sanitizer
NDC: 80018-101 | Form: LIQUID
Manufacturer: Bellwishes Corporation
Category: otc | Type: HUMAN OTC DRUG LABEL
Date: 20210210

ACTIVE INGREDIENTS: DIDECYLDIMONIUM BROMIDE 0.1 g/100 mL
INACTIVE INGREDIENTS: LOUREIRIN B; LEUCONOSTOC/RADISH ROOT FERMENT FILTRATE

Active Ingredient(s)

DIDECYLDIMONIUM BROMIDE 0.1%, Purpose: Antiseptic

Purpose

Antiseptic, Hand Sanitizer

Use

Hand Sanitizer to help reduce bacteria that potentially can cause disease. For use when soap and water are not available.

Warnings

For external use only.

Do not use

- in children less than 2 months of age
- on open skin wounds

When using this product keep out of eyes, ears, and mouth. In case of contact with eyes, rinse eyes thoroughly with water.
Stop use and ask a doctor if irritation or rash occurs. These may be signs of a serious condition.
Keep out of reach of children. If swallowed, get medical help or contact a Poison Control Center right away.

Stop use and ask a doctor if irritation or rash occurs. These may be signs of a serious condition.

Keep out of reach of children. If swallowed, get medical help or contact a Poison Control Center right away.

Directions

- Place enough product on hands to cover all surfaces. Rub hands together until dry.
- Supervise children under 6 years of age when using this product to avoid swallowing.

Other information

- Store between 15-30C (59-86F)
- Avoid freezing and excessive heat above 40C (104F)

Inactive ingredients

leuconostoc/radish root ferment, loureirin B, purified water USP

Package Label - Principal Display Panel

60 ml NDC: 80018-101-01

300 ml NDC: 80018-101-02

300 ml refill NDC: 80018-101-03